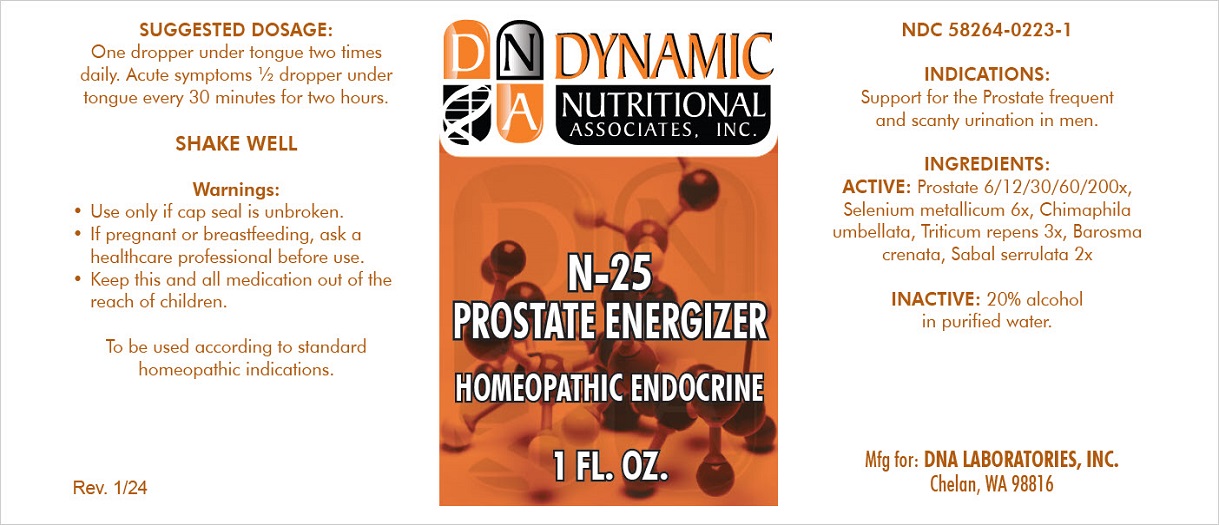 DRUG LABEL: N-25
NDC: 58264-0223 | Form: SOLUTION
Manufacturer: DNA Labs, Inc.
Category: homeopathic | Type: HUMAN OTC DRUG LABEL
Date: 20250129

ACTIVE INGREDIENTS: SERENOA REPENS WHOLE 2 [hp_X]/1 mL; AGATHOSMA CRENULATA WHOLE 2 [hp_X]/1 mL; CHIMAPHILA UMBELLATA 3 [hp_X]/1 mL; ELYMUS REPENS WHOLE 3 [hp_X]/1 mL; SELENIUM 6 [hp_X]/1 mL; BOS TAURUS PROSTATE GLAND 200 [hp_X]/1 mL
INACTIVE INGREDIENTS: ALCOHOL; WATER

N-25

NDC 58264-0223-1

INDICATIONS

PURPOSE

Support for the Prostate frequent and scanty urination in men.

INGREDIENTS

ACTIVE

Sabal serrulata 2x, Barosma crenata 2x, Chimaphila umbellata 3x, Triticum repens 3x, Selenium metallicum 6x, Prostate 6/12/30/60/200x

INACTIVE

20% alcohol in purified water.

SUGGESTED DOSAGE

One dropper under tongue two times daily. Acute symptoms ½ dropper under tongue every 30 minutes for two hours.

SHAKE WELL

Warnings

WHEN USING

- Use only if cap seal is unbroken.

PREGNANCY OR BREAST FEEDING

- If pregnant or breastfeeding, ask a healthcare professional before use.

KEEP OUT OF REACH OF CHILDREN

- Keep this and all medication out of the reach of children.

To be used according to standard homeopathic indications.

PRINCIPAL DISPLAY PANEL - 1 FL. OZ. Bottle Label

DYNAMIC
NUTRITIONAL
ASSOCIATES, INC.

N-25
PROSTATE ENERGIZER

HOMEOPATHIC ENDOCRINE

1 FL. OZ.